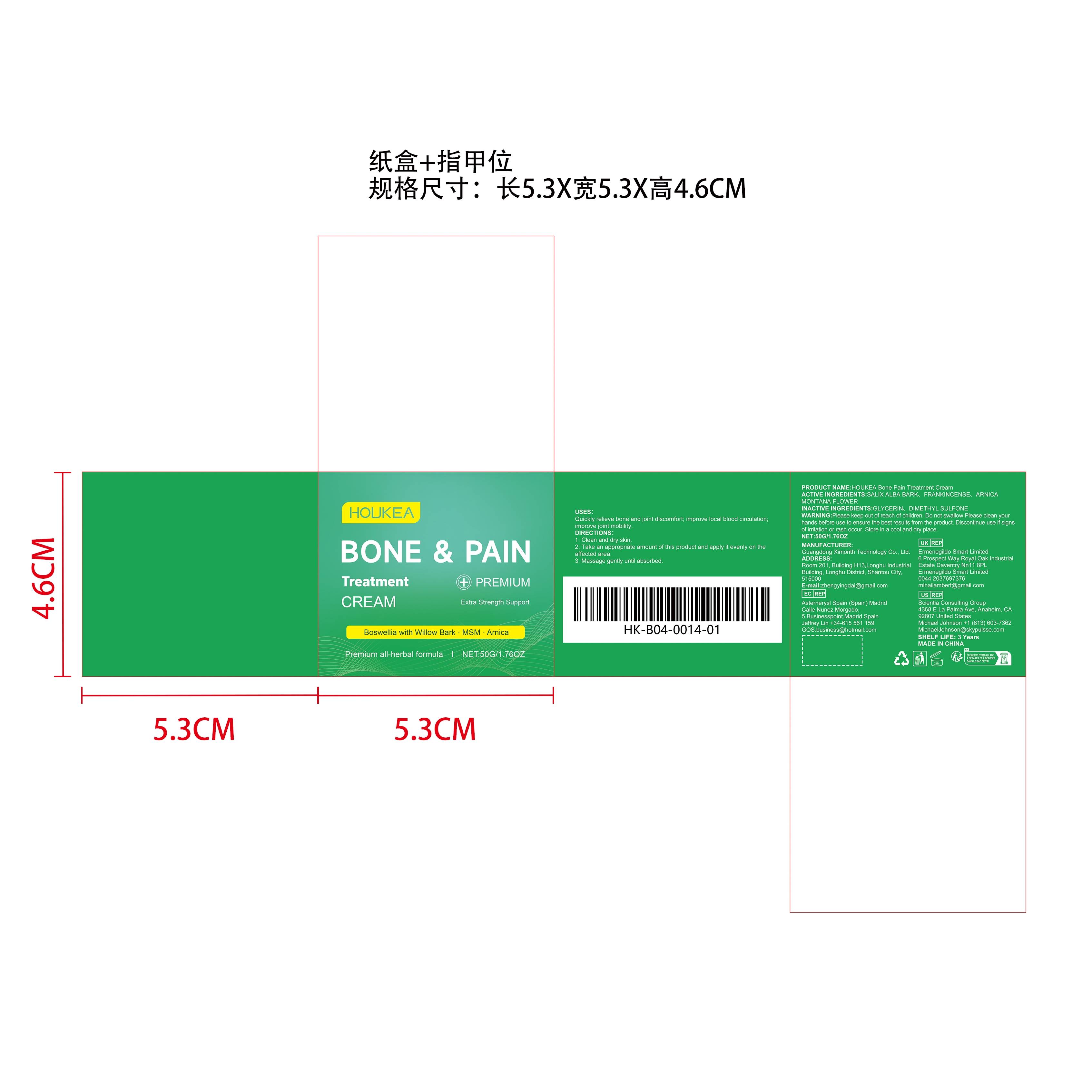 DRUG LABEL: HOUKEA Bone Pain Treatment Cream
NDC: 84660-100 | Form: CREAM
Manufacturer: Guangdong Ximonth Technology Co., Ltd.
Category: otc | Type: HUMAN OTC DRUG LABEL
Date: 20241031

ACTIVE INGREDIENTS: ARNICA MONTANA FLOWER 10 g/50 g; SALIX ALBA BARK 15 g/50 g; FRANKINCENSE 10 g/50 g
INACTIVE INGREDIENTS: GLYCERIN 10 g/50 g; DIMETHYL SULFONE 5 g/50 g

Active Ingredient(s)

SALIX ALBA BARK、FRANKINCENSE、ARNICA MONTANA FLOWER

Purpose

Quickly relieve bone and joint discomfort; improve local blood circulation; improve joint mobility.

Use

1. Clean and dry skin.
2. Take an appropriate amount of this product and apply it evenly on the affected area.
3. Massage gently until absorbed.

Warnings

Please keep out of reach of children.Do not swallow.Please clean your hands before use to ensure the best results from the product.Discontinue use if signs of irritation or rash occur.Store in a cool and dry place.

Do not use

Discontinue use if signs of irritation or rash occur.

Stop Use

Discontinue use if signs of irritation or rash occur.

KEEP OUT OF REACH OF CHILDREN

Please keep out of reach of children. Do not swallow.

SAFE HANDLING WARNING

Store in a cool and dry place.

INACTIVE INGREDIENT

GLYCERIN、DIMETHYL SULFONE